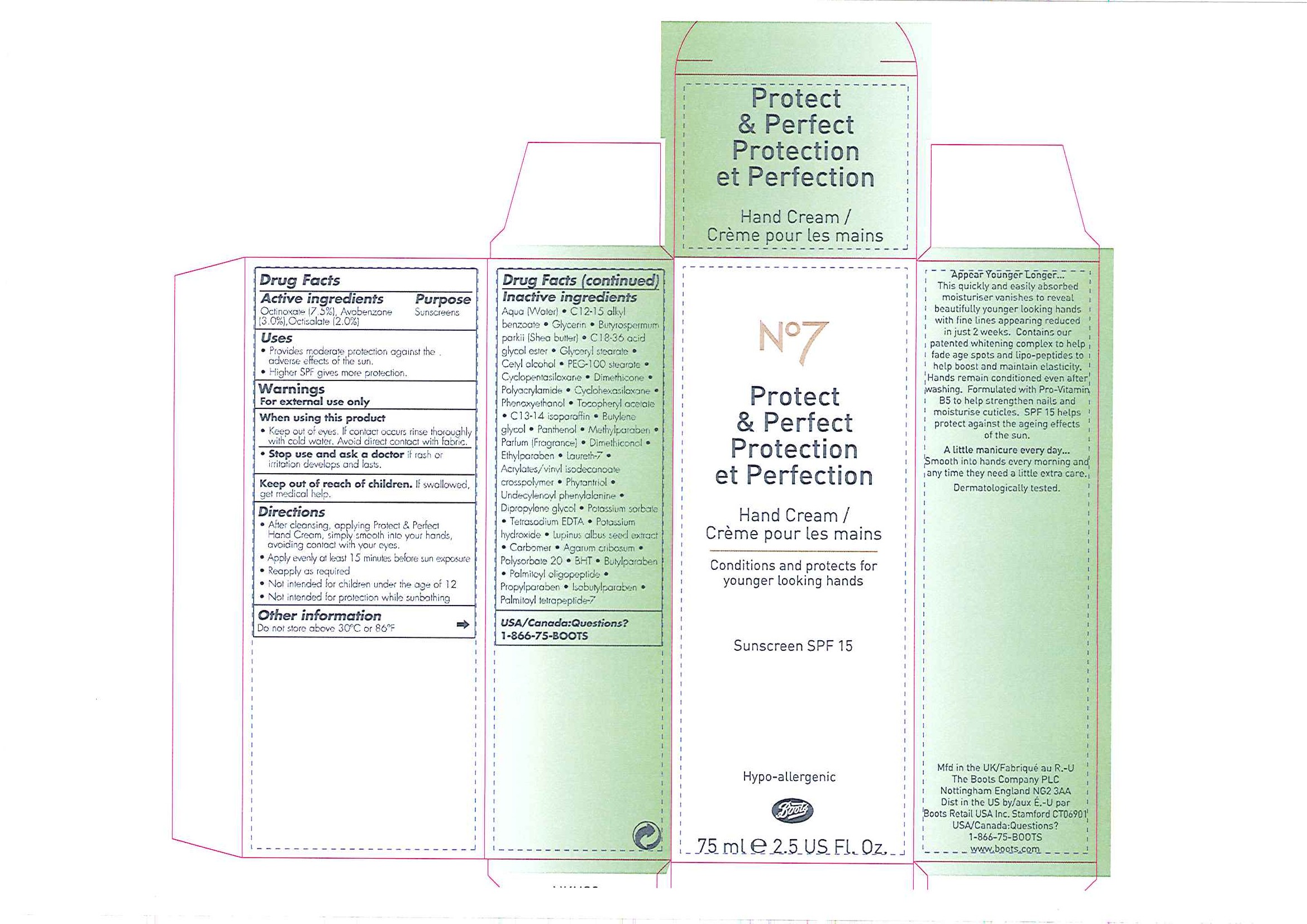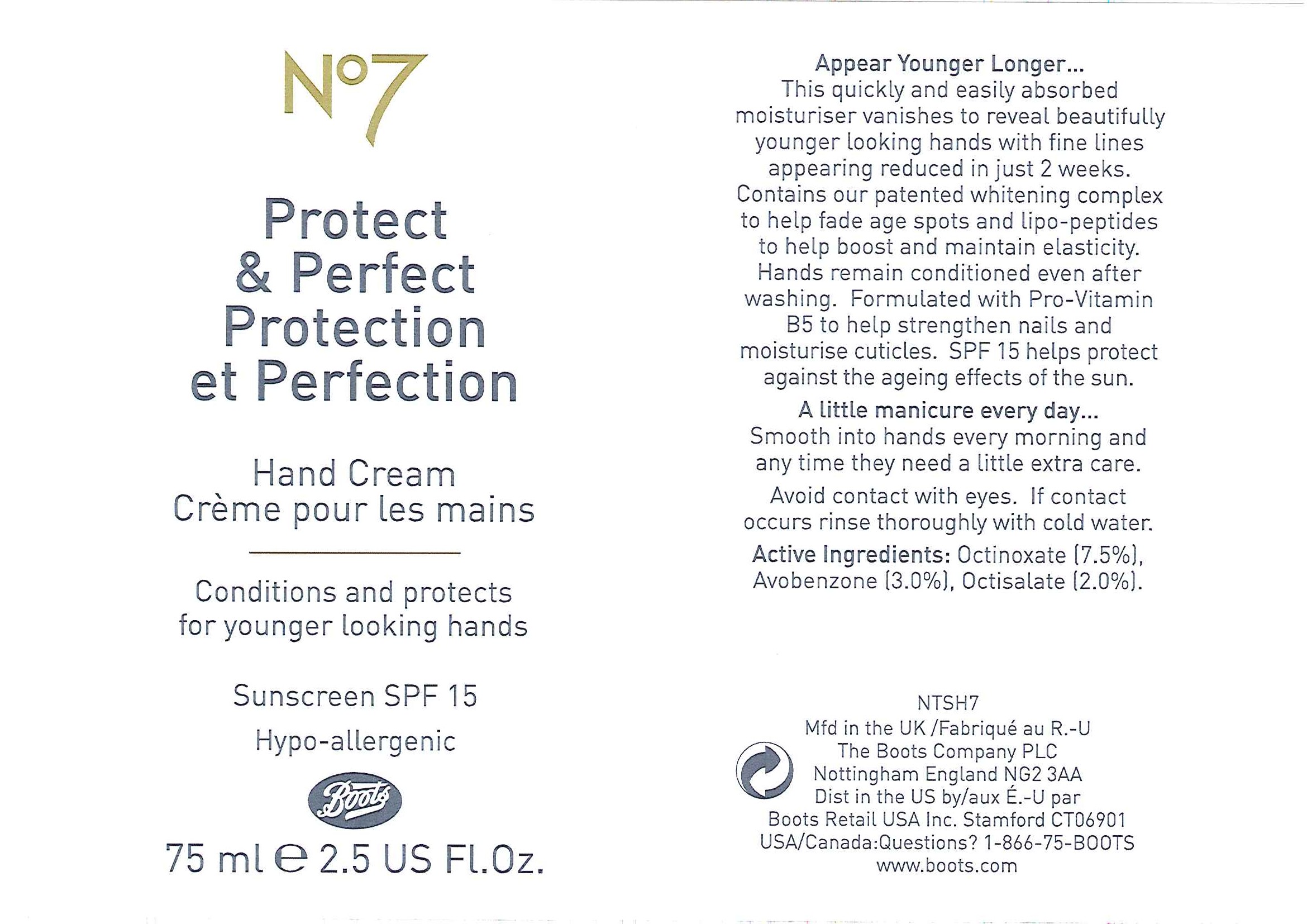 DRUG LABEL: No7 Protect and Perfect Hand Sunscreen SPF 15
NDC: 11489-068 | Form: CREAM
Manufacturer: BCM Ltd
Category: otc | Type: HUMAN OTC DRUG LABEL
Date: 20101202

ACTIVE INGREDIENTS: OCTINOXATE 5.625 mL/75 mL; AVOBENZONE 2.25 mL/75 mL; OCTISALATE 1.5 mL/75 mL
INACTIVE INGREDIENTS: WATER; GLYCERIN; SHEA BUTTER; GLYCERYL MONOSTEARATE; CETYL ALCOHOL; CYCLOMETHICONE 5; DIMETHICONE; CYCLOMETHICONE 6; PHENOXYETHANOL; .ALPHA.-TOCOPHEROL ACETATE, DL-; BUTYLENE GLYCOL; PANTHENOL; METHYLPARABEN; ETHYLPARABEN; POTASSIUM SORBATE; POTASSIUM HYDROXIDE; CARBOMER HOMOPOLYMER TYPE C; POLYSORBATE 20; BUTYLATED HYDROXYTOLUENE; BUTYLPARABEN; PROPYLPARABEN

Carton and tube labelling

ACTIVE INGREDIENT

NO7 PROTECT AND PERFECT HAND CREAM SUNSCREEN SPF 15

Active ingredients Purpose

Octinoxate (7.5%) Sunscreens

Avobenzone (3.0%)

Octisalate (2.0%)

Uses

- Provides moderate protection against the adverse effects of the sun
- Higher SPF gives more protection

Warnings

For external use only

When using this product

- Keep out of eyes. If contact occurs rinse thoroughly with cold water. Avoid direct contact with fabric.

Stop use and ask a doctor if rash or irritation develops and lasts.

KEEP OUT OF REACH OF CHILDREN

Keep our of reach of children. If swallowed, get medical help.

Directions

- After cleansing, applying Protect and Perfect Hand Cream, simply smooth into your hands, avoiding contact your eyes.
- Apply evenly at least 15 minutes before sun exposure
- Reapply as required
- Not intended for children under the age of 12
- Not intended for protection while sunbathing

Other information

Do not store above 30oC or 86oF

Inactive ingredients

Aqua (Water), C12-15 alkyl benzoate, Glycerin, Butyrospermum parkii (Shea butter), C18-36 acid glycol ester, Glyceryl stearate, Cetyl alcohol, PEG-100 stearate, Cyclopentasiloxane, Polyacrylamide, Cyclohexasiloxane, Phenoxyethanol, Tocopheryl acetate, C13-14 isoparaffin, Butylene glycol, Panthenol, Methylparaben, Parfum (Fragrance), Dimethiconol, Ethylparaben, Laureth-7, Acrylates/vinyl isodecanoate crosspolymer, Phytantriol, Undecylenoyl phenylalanine, Dipropylene glycol, Potassium sorbate, Tetrasodium EDTA, Potassium hydroxide, Lupinus albus seed extract, Carbomer, Agarum cribosum, Polysorbate 20, BHT, Butylparaben, Palmitoyl oligopeptide, Propylparaben, Isobutylparaben, Palmitoyl tetrapeptide-7

USA/Canada: Questions? 1-866-75-BOOTS

DESCRIPTION

Appear Younger Longer...
This quickly and easily absorbed moisturiser vanishes to reveal beautifully younger looking hands with fine lines appearing reduced in just 2 weeks. Contains our patented whitening complex to help fade age spots and lipo-peptides to help boost and maintain elasticity. Hands remain conditioned even after washing. Formulated with Pro-Vitamin B5 to help strengthen nails and moisturise cuticles. SPF 15 helps protect against the ageing effects of the sun.
A little manicure every day ...
Smooth into hands every morning and any time they need a little extra care.
Dermatologically tested

PATIENT COUNSELING INFORMATION

Mfd in the UK/Fabriqué au R.-U

The Boots Company PLC Nottingham England NG2 3AA

Dist in the US by/aux É.-U par

Boots Retail USA Inc. Stamford CT06901

USA/Canada: Questions? 1-866-75-Boots

www.boots.com

DESCRIPTION

Tube label

Appear Young Longer...
This quickly and easily absorbed moisturiser vanishes to reveal beautifully younger looking hands with fine lines appearing reduced in just 2 weeks. Contains our patented whitening complex to help fade age spots and lipo-peptides to help boost and maintain elasticity. Hands remain conditioned even after washing. Formulated with Pro-Vitamin B5 to help strengthen nails and moisturise cuticles. SPF 15 helps protect against the ageing effects of the sun.
A little manicure every day...
Smooth into hands every morning and any time they need a little extra care.
Avoid contact with eyes. If contact occurs rinse thoroughly with cold water.

Active Ingredients:

Octinoxate (7.5%), Avobenzone (3.0%), Octisalate (2.0%)

PATIENT COUNSELING INFORMATION

Mdf in the UK for/Fabriqué au R.-U.

The Boots Company PLC Nottingham England NG2 3AA

Dist in the USA by/aux É.U. par Boots Retail USA Inc. Stamford CT06901

USA/Canada: Questions? 1-866-75-BOOTS
www.boots.com

Carton label

No7 Protect and Perfect

Protection et Perfection

Hand Cream/Crème pour les mains

Conditions and protects for younger looking hands

Sunscreen SPF 15
Hypo-allergenic
Boots
75ml e 2.5 US Fl. Oz
P and P Hand Cream carton.jpg

Tube label

No7

Protect and Perfect

Protection et Perfection

Hand Cream

Crème pour les mains

Conditions and protects for younger looking hands

Sunscreen SPF 15

Hypo-allergenic

Boots

75ml e 2.5 US Fl. Oz

P and P Hand Cream tube.jpg